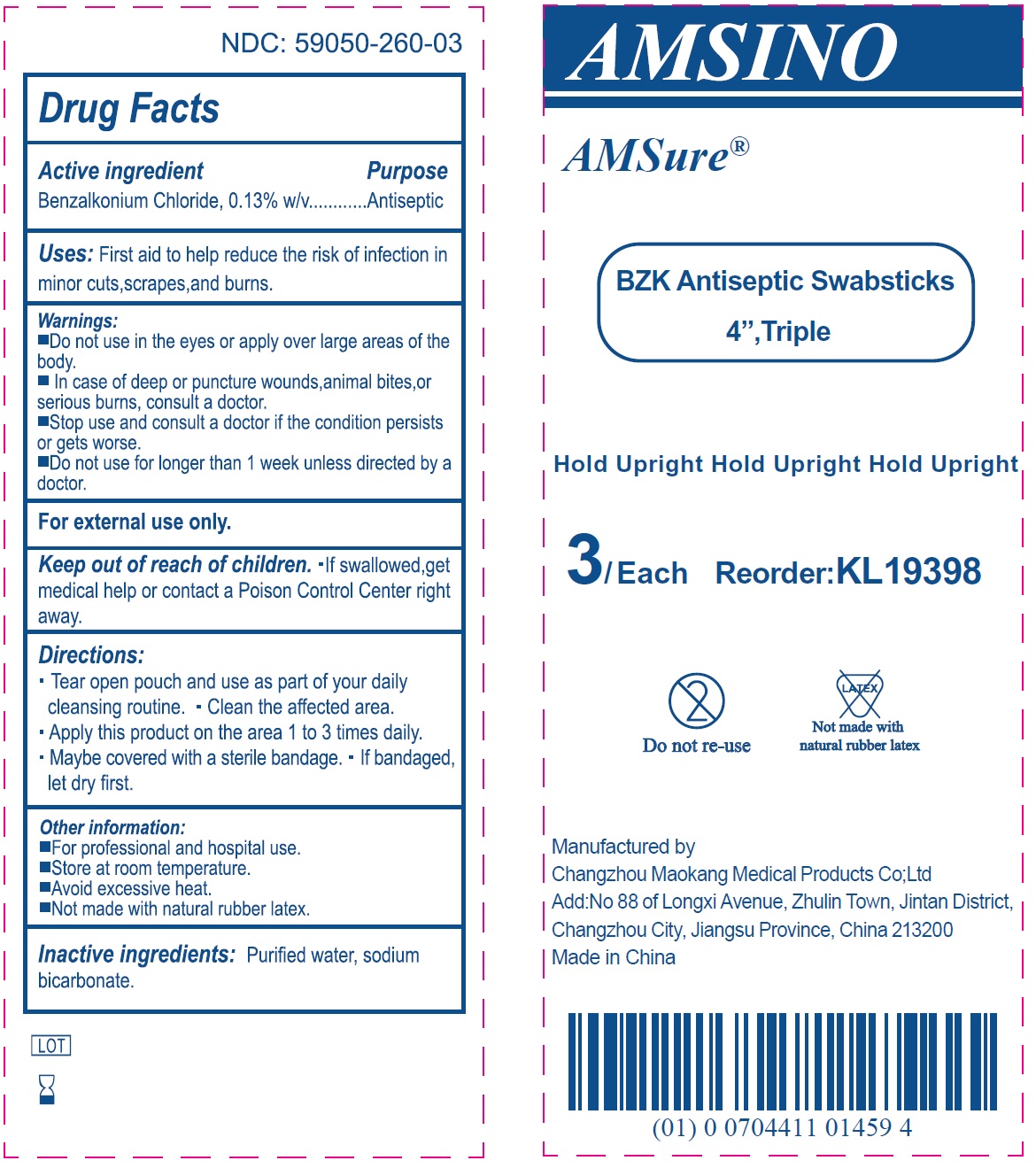 DRUG LABEL: BZK Antiseptic Swabsticks 4 Triple
NDC: 59050-260 | Form: LIQUID
Manufacturer: Changzhou Maokang Medical Products Co., Ltd
Category: otc | Type: HUMAN OTC DRUG LABEL
Date: 20241121

ACTIVE INGREDIENTS: BENZALKONIUM CHLORIDE 1.3 mg/1 g
INACTIVE INGREDIENTS: WATER; SODIUM BICARBONATE

BZK Antiseptic Swabsticks 4" Triple

Active ingredient

Benzalkonium Chloride, 0.13% w/v

Purpose

Antiseptic

Uses:

First aid to help reduce the risk of infection in minor cuts,scrapes,and burns.

Warnings:

- Do not use in the eyes or apply over large areas of the body.
- In case of deep or puncture wounds,animal bites,or serious burns, consult a doctor.

Stop use and consult a doctor

- if the condition persists or gets worse.

Do not use

- for longer than 1 week unless directed by a doctor.

For external use only.

Keep out of reach of children.

If swallowed,get medical help or contact a Poison Control Center right away.

Directions:

- Tear open pouch and use as part of your daily cleansing routine.
- Clean the affected area.
- Apply this product on the area 1 to 3 times daily.
- Maybe covered with a sterile bandage.
- If bandaged, let dry first.

Other information:

- For professional and hospital use.
- Store at room temperature.
- Avoid excessive heat.
- Not made with natural rubber latex.

Inactive ingredients:

Purified water, sodium bicarbonate.